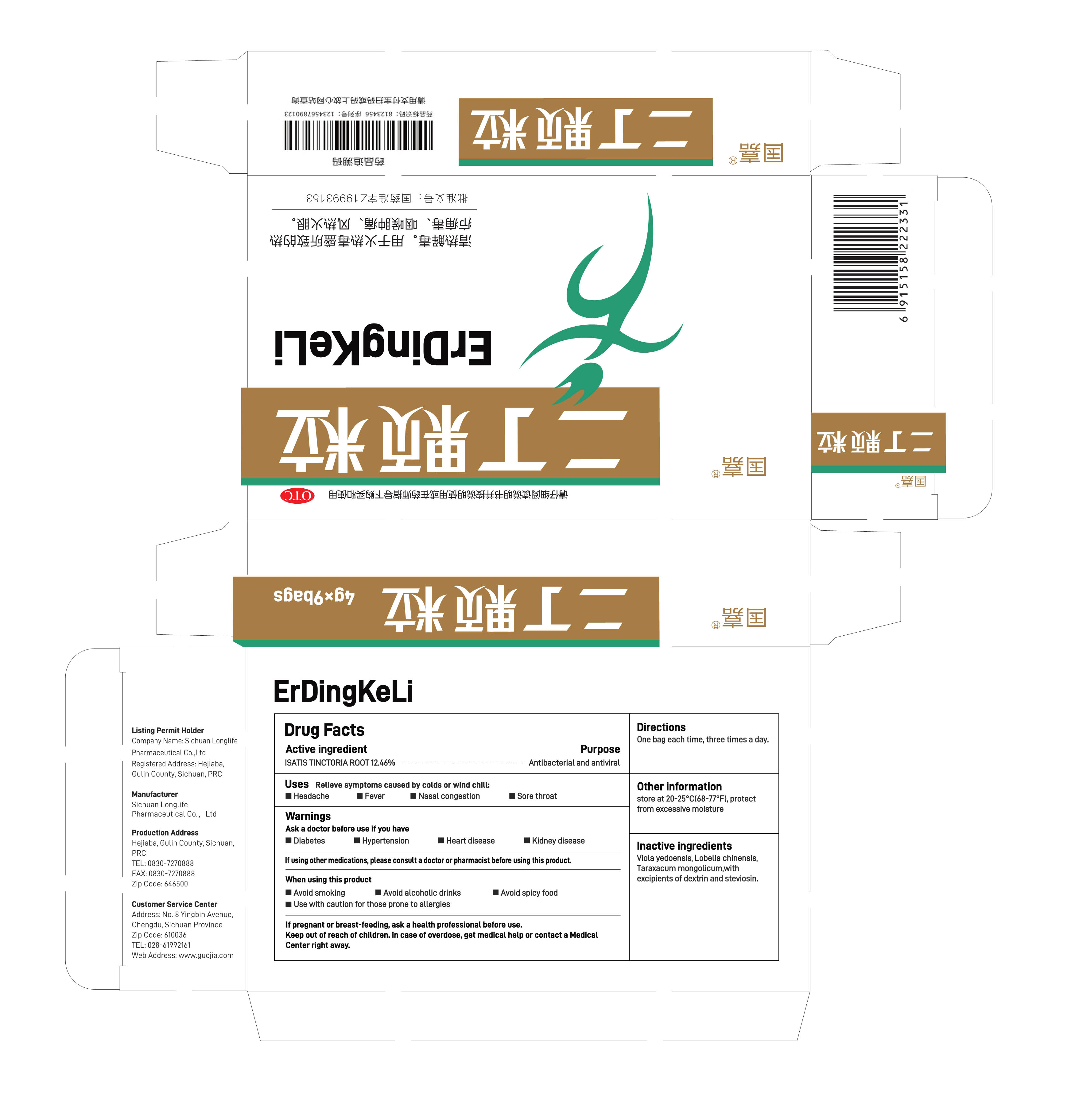 DRUG LABEL: ErDingKeLi
NDC: 84360-001 | Form: GRANULE
Manufacturer: Sichuan Longlife Pharmaceutical Co.,Ltd
Category: otc | Type: HUMAN OTC DRUG LABEL
Date: 20240529

ACTIVE INGREDIENTS: ISATIS TINCTORIA ROOT 12.46 g/100 g
INACTIVE INGREDIENTS: TARAXACUM MONGOLICUM; VIOLA PHILIPPICA WHOLE; STEVIOSIDE; LOBELIA CHINENSIS TOP; ICODEXTRIN

84360-001

ACTIVE INGREDIENT

ISATIS TINCTORIA ROOT 12.46%

PURPOSE

Antibacterial and antiviral

INDICATIONS AND USAGE

Relieve symptoms caused by colds or wind chill:
Headache

Fever
Nasal congestion
Sore throat

Ask a doctor before use if you have
Diabetes
Hypertension
Heart disease
Kidney disease

DO NOT USE

If using other medications, please consult a doctor or pharmacist before using this product.

When using this product
Avoid smoking
Avoid alcoholic drinks
Avoid spicy food
Use with caution for those prone to allergies

If pregnant or breast-feeding, ask a health professional before use.

STOP USE

in case of overdose, get medical help or contact a Medical Center right away

Keep out of reach of children.

DOSAGE AND ADMINISTRATION

One bag each time, three times a day.

STORAGE AND HANDLING

store at 20-25°C(68-77°F), protect from excessive moisture

INACTIVE INGREDIENT

Viola yedoensis, Lobelia chinensis, Taraxacum mongolicum,with excipients of dextrin and steviosin.